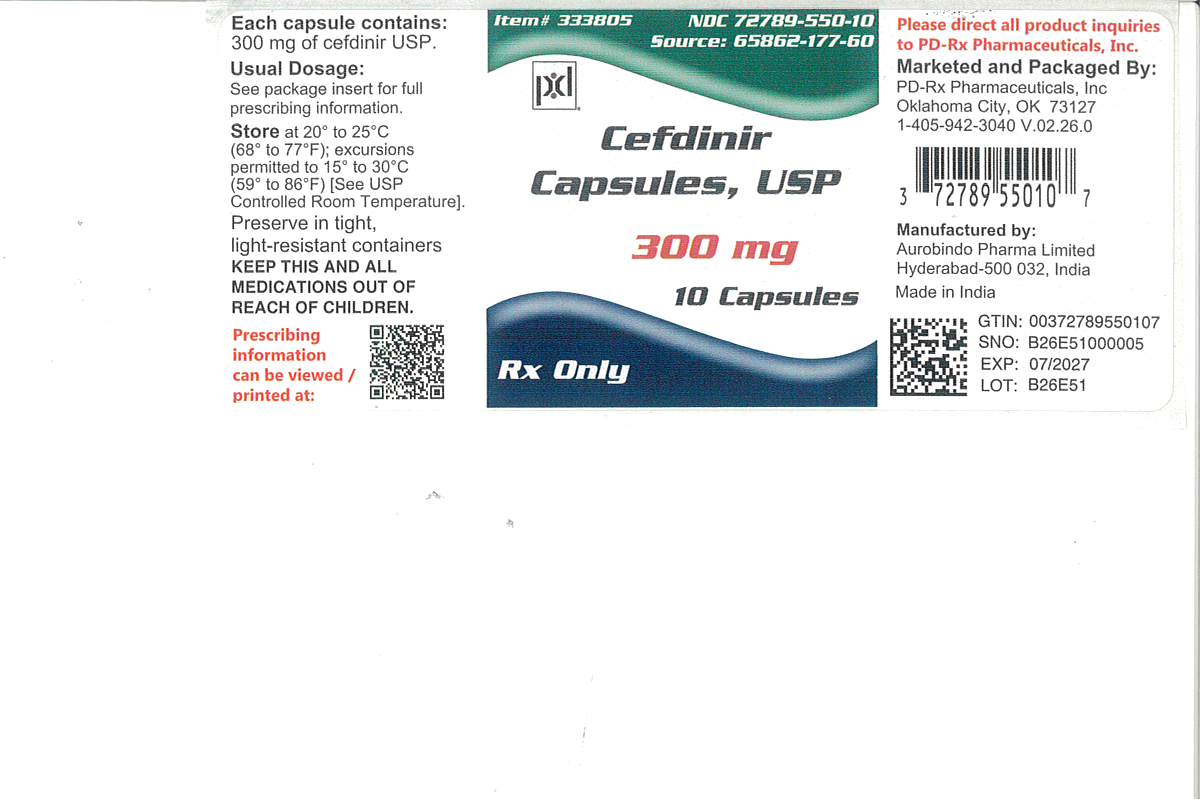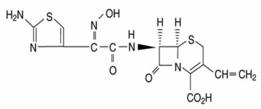 DRUG LABEL: Cefdinir
NDC: 72789-550 | Form: CAPSULE
Manufacturer: PD-Rx Pharmaceuticals, Inc.
Category: prescription | Type: HUMAN PRESCRIPTION DRUG LABEL
Date: 20260224

ACTIVE INGREDIENTS: CEFDINIR 300 mg/1 1
INACTIVE INGREDIENTS: CARBOXYMETHYLCELLULOSE CALCIUM; SILICON DIOXIDE; MAGNESIUM STEARATE; FD&C BLUE NO. 1; D&C RED NO. 28; TITANIUM DIOXIDE; GELATIN, UNSPECIFIED; SODIUM LAURYL SULFATE; FERROSOFERRIC OXIDE; SHELLAC

Cefdinir Capsules, USP
Rx only

To reduce the development of drug-resistant bacteria and maintain the effectiveness of cefdinir and other antibacterial drugs, cefdinir should be used only to treat or prevent infections that are proven or strongly suspected to be caused by bacteria.

DESCRIPTION

Cefdinir capsules, USP contain the active ingredient cefdinir, an extended-spectrum, semisynthetic cephalosporin, for oral administration. Chemically, cefdinir is [6R-[6α, 7β (Z)]]-7-[[(2-amino-4-thiazolyl)(hydroxyimino)acetyl]amino]-3-ethenyl-8-oxo-5-thia-1-azabicyclo[4.2.0]oct-2-ene-2-carboxylic acid. Cefdinir USP is a white to slightly brownish-yellow solid. It is slightly soluble in dilute hydrochloric acid and sparingly soluble in 0.1 M pH 7.0 phosphate buffer. The molecular formula is C14H13N5O5S2and the molecular weight is 395.42. Cefdinir has the structural formula shown below:

Cefdinir capsules, USP contain 300 mg cefdinir USP and the following inactive ingredients: carboxymethylcellulose calcium, colloidal silicon dioxide and magnesium stearate. The empty hard gelatin capsule shells contain FD&C Blue #1, D&C Red #28, titanium dioxide, gelatin and sodium lauryl sulphate. The capsules are printed with edible ink containing black iron oxide and shellac.

CLINICAL PHARMACOLOGY

Pharmacokinetics and Drug Metabolism

Absorption

Oral Bioavailability

Maximal plasma cefdinir concentrations occur 2 to 4 hours postdose following capsule or suspension administration. Plasma cefdinir concentrations increase with dose, but the increases are less than dose-proportional from 300 mg (7 mg/kg) to 600 mg (14 mg/kg). Following administration of suspension to healthy adults, cefdinir bioavailability is 120% relative to capsules. Estimated bioavailability of cefdinir capsules is 21% following administration of a 300 mg capsule dose, and 16% following administration of a 600 mg capsule dose. Estimated absolute bioavailability of cefdinir suspension is 25%. Cefdinir oral suspension of 250 mg/5 mL strength was shown to be bioequivalent to the 125 mg/5 mL strength in healthy adults under fasting conditions.

Effect of Food

The Cmaxand AUC of cefdinir from the capsules are reduced by 16% and 10%, respectively, when given with a high-fat meal. In adults given the 250 mg/5 mL oral suspension with a high-fat meal, the Cmaxand AUC of cefdinir are reduced by 44% and 33%, respectively. The magnitude of these reductions is not likely to be clinically significant because the safety and efficacy studies of oral suspension in pediatric patients were conducted without regard to food intake. Therefore, cefdinir may be taken without regard to food.

Cefdinir Capsules

Cefdinir plasma concentrations and pharmacokinetic parameter values following administration of single 300 and 600 mg oral doses of cefdinir to adult subjects are presented in the following table:

Mean (±SD) Plasma Cefdinir Pharmacokinetic Parameter Values Following Administration of Capsules to Adult Subjects
Dose | Cmax (mcg/mL) | tmax (hr) | AUC (mcg•hr/mL)
300 mg | 1.6 (0.55) | 2.9 (0.89) | 7.05 (2.17)
600 mg | 2.87 (1.01) | 3 (0.66) | 11.1 (3.87)

Cefdinir Suspension

Cefdinir plasma concentrations and pharmacokinetic parameter values following administration of single 7 and 14 mg/kg oral doses of cefdinir to pediatric subjects (age 6 months to 12 years) are presented in the following table:

Mean (±SD) Plasma Cefdinir Pharmacokinetic Parameter Values Following Administration of Suspension to Pediatric Subjects
Dose | Cmax (mcg/mL) | tmax (hr) | AUC (mcg•hr/mL)
7 mg/kg | 2.3 (0.65) | 2.2 (0.6) | 8.31 (2.5)
14 mg/kg | 3.86 (0.62) | 1.8 (0.4) | 13.4 (2.64)

Multiple Dosing

Cefdinir does not accumulate in plasma following once- or twice-daily administration to subjects with normal renal function.

Distribution

The mean volume of distribution (Vdarea) of cefdinir in adult subjects is 0.35 L/kg (±0.29); in pediatric subjects (age 6 months to 12 years), cefdinir Vdareais 0.67 L/kg (±0.38). Cefdinir is 60% to 70% bound to plasma proteins in both adult and pediatric subjects; binding is independent of concentration.

Skin Blister

In adult subjects, median (range) maximal blister fluid cefdinir concentrations of 0.65 (0.33 to 1.1) and 1.1 (0.49 to 1.9) mcg/mL were observed 4 to 5 hours following administration of 300 and 600 mg doses, respectively. Mean (±SD) blister Cmaxand AUC(0-∞)values were 48% (±13) and 91% (±18) of corresponding plasma values.

Tonsil Tissue

In adult patients undergoing elective tonsillectomy, respective median tonsil tissue cefdinir concentrations 4 hours after administration of single 300 and 600 mg doses were 0.25 (0.22 to 0.46) and 0.36 (0.22 to 0.8) mcg/g. Mean tonsil tissue concentrations were 24% (±8) of corresponding plasma concentrations.

Sinus Tissue

In adult patients undergoing elective maxillary and ethmoid sinus surgery, respective median sinus tissue cefdinir concentrations 4 hours after administration of single 300 and 600 mg doses were <0.12 (<0.12 to 0.46) and 0.21 (<0.12 to 2) mcg/g. Mean sinus tissue concentrations were 16% (±20) of corresponding plasma concentrations.

Lung Tissue

In adult patients undergoing diagnostic bronchoscopy, respective median bronchial mucosa cefdinir concentrations 4 hours after administration of single 300 and 600 mg doses were 0.78 (<0.06 to 1.33) and 1.14 (<0.06 to 1.92) mcg/mL, and were 31% (±18) of corresponding plasma concentrations. Respective median epithelial lining fluid concentrations were 0.29 (<0.3 to 4.73) and 0.49 (<0.3 to 0.59) mcg/mL, and were 35% (±83) of corresponding plasma concentrations.

Middle Ear Fluid

In 14 pediatric patients with acute bacterial otitis media, respective median middle ear fluid cefdinir concentrations 3 hours after administration of single 7 and 14 mg/kg doses were 0.21 (<0.09 to 0.94) and 0.72 (0.14 to 1.42) mcg/mL. Mean middle ear fluid concentrations were 15% (±15) of corresponding plasma concentrations.

CSF

Data on cefdinir penetration into human cerebrospinal fluid are not available.

Metabolism and Excretion

Cefdinir is not appreciably metabolized. Activity is primarily due to parent drug. Cefdinir is eliminated principally via renal excretion with a mean plasma elimination half-life (t½) of 1.7 (±0.6) hours. In healthy subjects with normal renal function, renal clearance is 2 (±1) mL/min/kg, and apparent oral clearance is 11.6 (±6) and 15.5 (±5.4) mL/min/kg following doses of 300 and 600 mg, respectively. Mean percent of dose recovered unchanged in the urine following 300 and 600 mg doses is 18.4% (±6.4) and 11.6% (±4.6), respectively. Cefdinir clearance is reduced in patients with renal dysfunction (see Special Populations: Patients with Renal Insufficiency).
Because renal excretion is the predominant pathway of elimination, dosage should be adjusted in patients with markedly compromised renal function or who are undergoing hemodialysis (see DOSAGE AND ADMINISTRATION).

Special Populations

Patients with Renal Insufficiency

Cefdinir pharmacokinetics were investigated in 21 adult subjects with varying degrees of renal function. Decreases in cefdinir elimination rate, apparent oral clearance (CL/F), and renal clearance were approximately proportional to the reduction in creatinine clearance (CLcr). As a result, plasma cefdinir concentrations were higher and persisted longer in subjects with renal impairment than in those without renal impairment. In subjects with CLcrbetween 30 and 60 mL/min, Cmaxand t½increased by approximately 2-fold and AUC by approximately 3-fold. In subjects with CLcr<30 mL/min, Cmaxincreased by approximately 2-fold, t½by approximately 5-fold, and AUC by approximately 6-fold. Dosage adjustment is recommended in patients with markedly compromised renal function (creatinine clearance <30 mL/min; see DOSAGE AND ADMINISTRATION).

Hemodialysis

Cefdinir pharmacokinetics were studied in 8 adult subjects undergoing hemodialysis. Dialysis (4 hours duration) removed 63% of cefdinir from the body and reduced apparent elimination t½from 16 (±3.5) to 3.2 (±1.2) hours. Dosage adjustment is recommended in this patient population (see DOSAGE AND ADMINISTRATION).

Hepatic Disease

Because cefdinir is predominantly renally eliminated and not appreciably metabolized, studies in patients with hepatic impairment were not conducted. It is not expected that dosage adjustment will be required in this population.

Geriatric Patients

The effect of age on cefdinir pharmacokinetics after a single 300 mg dose was evaluated in 32 subjects 19 to 91 years of age. Systemic exposure to cefdinir was substantially increased in older subjects (N=16), Cmaxby 44% and AUC by 86%. This increase was due to a reduction in cefdinir clearance. The apparent volume of distribution was also reduced, thus no appreciable alterations in apparent elimination t½were observed (elderly: 2.2 ± 0.6 hours vs young: 1.8 ± 0.4 hours). Since cefdinir clearance has been shown to be primarily related to changes in renal function rather than age, elderly patients do not require dosage adjustment unless they have markedly compromised renal function (creatinine clearance <30 mL/min, see Patients with Renal Insufficiency, above).

Gender and Race

The results of a meta-analysis of clinical pharmacokinetics (N=217) indicated no significant impact of either gender or race on cefdinir pharmacokinetics.

Microbiology

Mechanism of Action
As with other cephalosporins, bactericidal activity of cefdinir results from inhibition of cell wall synthesis. Cefdinir is stable in the presence of some, but not all, β-lactamase enzymes. As a result, many organisms resistant to penicillins and some cephalosporins are susceptible to cefdinir.
Mechanism of Resistance
Resistance to cefdinir is primarily through hydrolysis by some β-lactamases, alteration of penicillin-binding proteins (PBPs) and decreased permeability. Cefdinir is inactive against most strains of Enterobacterspp., Pseudomonasspp., Enterococcusspp., penicillin-resistant streptococci, and methicillin-resistant staphylococci. β-lactamase negative, ampicillin-resistant (BLNAR) H. influenzaestrains are typically non-susceptible to cefdinir.
Antimicrobial Activity
Cefdinir has been shown to be active against most strains of the following microorganisms, both in vitroand in clinical infections as described in INDICATIONS AND USAGE.

Gram-Positive Bacteria

Staphylococcus aureus(methicillin-susceptible strains only)
Streptococcus pneumoniae(penicillin-susceptible strains only)
Streptococcus pyogenes

Gram-Negative Bacteria

Haemophilus influenzae
Haemophilus parainfluenzae
Moraxella catarrhalis
The following in vitrodata are available, but their clinical significance is unknown.
Cefdinir exhibits in vitrominimum inhibitory concentrations (MICs) of 1 mcg/mL or less against (≥90%) strains of the following microorganisms; however, the safety and effectiveness of cefdinir in treating clinical infections due to these microorganisms have not been established in adequate and well-controlled clinical trials.

Gram-Positive Bacteria

Staphylococcus epidermidis(methicillin-susceptible strains only)
Streptococcus agalactiae
Viridans group streptococci

Gram-Negative Bacteria

Citrobacter koseri
Escherichia coli
Klebsiella pneumoniae
Proteus mirabilis

Susceptibility Testing
For specific information regarding susceptibility test interpretive criteria and associated test methods and quality control standards recognized by FDA for this drug, please see: https://www.fda.gov/STIC.

INDICATIONS AND USAGE

To reduce the development of drug-resistant bacteria and maintain the effectiveness of cefdinir and other antibacterial drugs, cefdinir should be used only to treat or prevent infections that are proven or strongly suspected to be caused by susceptible bacteria. When culture and susceptibility information are available, they should be considered in selecting or modifying antibacterial therapy. In the absence of such data, local epidemiology and susceptibility patterns may contribute to the empiric selection of therapy.
Cefdinir capsules, USP are indicated for the treatment of patients with mild to moderate infections caused by susceptible strains of the designated microorganisms in the conditions listed below.

Adults and Adolescents

Community-Acquired Pneumoniacaused by Haemophilus influenzae(including β-lactamase producing strains), Haemophilus parainfluenzae(including β-lactamase producing strains), Streptococcus pneumoniae(penicillin-susceptible strains only), and Moraxella catarrhalis(including β-lactamase producing strains) (see CLINICAL STUDIES).
Acute Exacerbations of Chronic Bronchitiscaused by Haemophilus influenzae(including β-lactamase producing strains), Haemophilus parainfluenzae(including β-lactamase producing strains), Streptococcus pneumoniae(penicillin-susceptible strains only), and Moraxella catarrhalis(including β-lactamase producing strains).
Acute Maxillary Sinusitiscaused by Haemophilus influenzae(including β-lactamase producing strains), Streptococcus pneumoniae(penicillin-susceptible strains only), and Moraxella catarrhalis(including β-lactamase producing strains).
NOTE:For information on use in pediatric patients, see Pediatric Useand DOSAGE AND ADMINISTRATION.
Pharyngitis/Tonsillitis caused by Streptococcus pyogenes(see CLINICAL STUDIES).
NOTE:Cefdinir is effective in the eradication of S. pyogenesfrom the oropharynx. Cefdinir has not, however, been studied for the prevention of rheumatic fever following S. pyogenespharyngitis/tonsillitis. Only intramuscular penicillin has been demonstrated to be effective for the prevention of rheumatic fever.
Uncomplicated Skin and Skin Structure Infections caused by Staphylococcus aureus(including β-lactamase producing strains) and Streptococcus pyogenes.

Pediatric Patients

Acute Bacterial Otitis Mediacaused by Haemophilus influenzae(including β-lactamase producing strains), Streptococcus pneumoniae(penicillin-susceptible strains only), and Moraxella catarrhalis(including β-lactamase producing strains).
Pharyngitis/Tonsillitis caused by Streptococcus pyogenes(see CLINICAL STUDIES).
NOTE: Cefdinir is effective in the eradication of S. pyogenesfrom the oropharynx. Cefdinir has not, however, been studied for the prevention of rheumatic fever following S. pyogenespharyngitis/tonsillitis. Only intramuscular penicillin has been demonstrated to be effective for the prevention of rheumatic fever.
Uncomplicated Skin and Skin Structure Infections caused by Staphylococcus aureus(including β-lactamase producing strains) and Streptococcus pyogenes.

CONTRAINDICATIONS

Cefdinir capsules are contraindicated in patients with known allergy to the cephalosporin class of antibiotics.

WARNINGS

BEFORE THERAPY WITH CEFDINIR IS INSTITUTED, CAREFUL INQUIRY SHOULD BE MADE TO DETERMINE WHETHER THE PATIENT HAS HAD PREVIOUS HYPERSENSITIVITY REACTIONS TO CEFDINIR, OTHER CEPHALOSPORINS, PENICILLINS, OR OTHER DRUGS. IF CEFDINIR IS TO BE GIVEN TO PENICILLIN-SENSITIVE PATIENTS, CAUTION SHOULD BE EXERCISED BECAUSE CROSS-HYPERSENSITIVITY AMONG β-LACTAM ANTIBIOTICS HAS BEEN CLEARLY DOCUMENTED AND MAY OCCUR IN UP TO 10% OF PATIENTS WITH A HISTORY OF PENICILLIN ALLERGY. IF AN ALLERGIC REACTION TO CEFDINIR OCCURS, THE DRUG SHOULD BE DISCONTINUED. SERIOUS ACUTE HYPERSENSITIVITY REACTIONS MAY REQUIRE TREATMENT WITH EPINEPHRINE AND OTHER EMERGENCY MEASURES, INCLUDING OXYGEN, INTRAVENOUS FLUIDS, INTRAVENOUS ANTIHISTAMINES, CORTICOSTEROIDS, PRESSOR AMINES, AND AIRWAY MANAGEMENT, AS CLINICALLY INDICATED.
Clostridium difficile associated diarrhea (CDAD) has been reported with use of nearly all antibacterial agents, including cefdinir, and may range in severity from mild diarrhea to fatal colitis. Treatment with antibacterial agents alters the normal flora of the colon leading to overgrowth of C. difficile.
C. difficile produces toxins A and B which contribute to the development of CDAD. Hypertoxin producing strains of C. difficilecause increased morbidity and mortality, as these infections can be refractory to antimicrobial therapy and may require colectomy. CDAD must be considered in all patients who present with diarrhea following antibacterial use. Careful medical history is necessary since CDAD has been reported to occur over two months after the administration of antibacterial agents.
If CDAD is suspected or confirmed, ongoing antibacterial use not directed against C. difficilemay need to be discontinued. Appropriate fluid and electrolyte management, protein supplementation, antibacterial treatment of C. difficile, and surgical evaluation should be instituted as clinically indicated.

PRECAUTIONS

General

Prescribing cefdinir in the absence of a proven or strongly suspected bacterial infection or a prophylactic indication is unlikely to provide benefit to the patient and increases the risk of the development of drug-resistant bacteria.
As with other broad-spectrum antibiotics, prolonged treatment may result in the possible emergence and overgrowth of resistant organisms. Careful observation of the patient is essential. If superinfection occurs during therapy, appropriate alternative therapy should be administered.
Cefdinir, as with other broad-spectrum antimicrobials (antibiotics), should be prescribed with caution in individuals with a history of colitis.
In patients with transient or persistent renal insufficiency (creatinine clearance <30 mL/min), the total daily dose of cefdinir should be reduced because high and prolonged plasma concentrations of cefdinir can result following recommended doses (see DOSAGE AND ADMINISTRATION).

Information for Patients

Patients should be counseled that antibacterial drugs including cefdinir should only be used to treat bacterial infections. They do not treat viral infections (e.g., the common cold). When cefdinir is prescribed to treat a bacterial infection, patients should be told that although it is common to feel better early in the course of therapy, the medication should be taken exactly as directed. Skipping doses or not completing the full course of therapy may (1) decrease the effectiveness of the immediate treatment and (2) increase the likelihood that bacteria will develop resistance and will not be treatable by cefdinir or other antibacterial drugs in the future.
Antacids containing magnesium or aluminum interfere with the absorption of cefdinir. If this type of antacid is required during cefdinir therapy, cefdinir should be taken at least 2 hours before or after the antacid.
Iron supplements, including multivitamins that contain iron, interfere with the absorption of cefdinir. If iron supplements are required during cefdinir therapy, cefdinir should be taken at least 2 hours before or after the supplement.
Iron-fortified infant formula does not significantly interfere with the absorption of cefdinir.
Diarrhea is a common problem caused by antibiotics which usually ends when the antibiotic is discontinued. Sometimes after starting treatment with antibiotics, patients can develop watery and bloody stools (with or without stomach cramps and fever) even as late as two or more months after having taken the last dose of the antibiotic. If this occurs, patients should contact their physician as soon as possible.

Drug Interactions

Antacids(aluminum- or magnesium-containing)

Concomitant administration of 300 mg cefdinir capsules with 30 mL Maalox®TC suspension reduces the rate (Cmax) and extent (AUC) of absorption by approximately 40%. Time to reach Cmaxis also prolonged by 1 hour. There are no significant effects on cefdinir pharmacokinetics if the antacid is administered 2 hours before or 2 hours after cefdinir. If antacids are required during cefdinir therapy, cefdinir should be taken at least 2 hours before or after the antacid.

Probenecid

As with other β-lactam antibiotics, probenecid inhibits the renal excretion of cefdinir, resulting in an approximate doubling in AUC, a 54% increase in peak cefdinir plasma levels, and a 50% prolongation in the apparent elimination t½.

Iron Supplements and Foods Fortified With Iron

Concomitant administration of cefdinir with a therapeutic iron supplement containing 60 mg of elemental iron (as FeSO4) or vitamins supplemented with 10 mg of elemental iron reduced extent of absorption by 80% and 31%, respectively. If iron supplements are required during cefdinir therapy, cefdinir should be taken at least 2 hours before or after the supplement.
The effect of foods highly fortified with elemental iron (primarily iron-fortified breakfast cereals) on cefdinir absorption has not been studied.
Concomitantly administered iron-fortified infant formula (2.2 mg elemental iron/6 oz) has no significant effect on cefdinir pharmacokinetics.
There have been reports of reddish stools in patients receiving cefdinir. In many cases, patients were also receiving iron-containing products. The reddish color is due to the formation of a nonabsorbable complex between cefdinir or its breakdown products and iron in the gastrointestinal tract.

Drug/Laboratory Test Interactions

A false-positive reaction for ketones in the urine may occur with tests using nitroprusside, but not with those using nitroferricyanide. The administration of cefdinir may result in a false-positive reaction for glucose in urine using Clinitest®, Benedict’s solution, or Fehling’s solution. It is recommended that glucose tests based on enzymatic glucose oxidase reactions (such as Clinistix®or Tes-Tape®) be used. Cephalosporins are known to occasionally induce a positive direct Coombs’ test.

Carcinogenesis, Mutagenesis, Impairment of Fertility

The carcinogenic potential of cefdinir has not been evaluated. No mutagenic effects were seen in the bacterial reverse mutation assay (Ames) or point mutation assay at the hypoxanthine-guanine phosphoribosyltransferase locus (HGPRT) in V79 Chinese hamster lung cells. No clastogenic effects were observed in vitroin the structural chromosome aberration assay in V79 Chinese hamster lung cells or in vivoin the micronucleus assay in mouse bone marrow. In rats, fertility and reproductive performance were not affected by cefdinir at oral doses up to 1000 mg/kg/day (70 times the human dose based on mg/kg/day, 11 times based on mg/m^2/day).

Pregnancy - Teratogenic Effects

Pregnancy Category B

Cefdinir was not teratogenic in rats at oral doses up to 1000 mg/kg/day (70 times the human dose based on mg/kg/day, 11 times based on mg/m^2/day) or in rabbits at oral doses up to 10 mg/kg/day (0.7 times the human dose based on mg/kg/day, 0.23 times based on mg/m^2/day). Maternal toxicity (decreased body weight gain) was observed in rabbits at the maximum tolerated dose of 10 mg/kg/day without adverse effects on offspring. Decreased body weight occurred in rat fetuses at ≥100 mg/kg/day, and in rat offspring at ≥32 mg/kg/day. No effects were observed on maternal reproductive parameters or offspring survival, development, behavior, or reproductive function.
There are, however, no adequate and well-controlled studies in pregnant women. Because animal reproduction studies are not always predictive of human response, this drug should be used during pregnancy only if clearly needed.

Labor and Delivery

Cefdinir has not been studied for use during labor and delivery.

Nursing Mothers

Following administration of single 600 mg doses, cefdinir was not detected in human breast milk.

Pediatric Use

Safety and efficacy in neonates and infants less than 6 months of age have not been established. Use of cefdinir for the treatment of acute maxillary sinusitis in pediatric patients (age 6 months through 12 years) is supported by evidence from adequate and well-controlled studies in adults and adolescents, the similar pathophysiology of acute sinusitis in adult and pediatric patients, and comparative pharmacokinetic data in the pediatric population.

Geriatric Use

Efficacy is comparable in geriatric patients and younger adults. While cefdinir has been well-tolerated in all age groups, in clinical trials geriatric patients experienced a lower rate of adverse events, including diarrhea, than younger adults. Dose adjustment in elderly patients is not necessary unless renal function is markedly compromised (see DOSAGE AND ADMINISTRATION).

ADVERSE EVENTS

Clinical Trials - Cefdinir Capsules (Adult and Adolescent Patients)

In clinical trials, 5093 adult and adolescent patients (3841 U.S. and 1252 non-U.S.) were treated with the recommended dose of cefdinir capsules (600 mg/day). Most adverse events were mild and self-limiting. No deaths or permanent disabilities were attributed to cefdinir. One hundred forty-seven of 5093 (3%) patients discontinued medication due to adverse events thought by the investigators to be possibly, probably, or definitely associated with cefdinir therapy. The discontinuations were primarily for gastrointestinal disturbances, usually diarrhea or nausea. Nineteen of 5093 (0.4%) patients were discontinued due to rash thought related to cefdinir administration.
In the U.S., the following adverse events were thought by investigators to be possibly, probably, or definitely related to cefdinir capsules in multiple-dose clinical trials (N = 3841 cefdinir-treated patients):

ADVERSE EVENTS ASSOCIATED WITH CEFDINIR CAPSULESU.S. TRIALS IN ADULT AND ADOLESCENT PATIENTS (N = 3841)a
Incidence ≥1% | Diarrhea | 15%
Incidence ≥1% | Vaginal moniliasis | 4% of women
Incidence ≥1% | Nausea | 3%
Incidence ≥1% | Headache | 2%
Incidence ≥1% | Abdominal pain | 1%
Incidence ≥1% | Vaginitis | 1% of women
Incidence <1% but >0.1% | Rash | 0.9%
Incidence <1% but >0.1% | Dyspepsia | 0.7%
Incidence <1% but >0.1% | Flatulence | 0.7%
Incidence <1% but >0.1% | Vomiting | 0.7%
Incidence <1% but >0.1% | Abnormal stools | 0.3%
Incidence <1% but >0.1% | Anorexia | 0.3%
Incidence <1% but >0.1% | Constipation | 0.3%
Incidence <1% but >0.1% | Dizziness | 0.3%
Incidence <1% but >0.1% | Dry mouth | 0.3%
Incidence <1% but >0.1% | Asthenia | 0.2%
Incidence <1% but >0.1% | Insomnia | 0.2%
Incidence <1% but >0.1% | Leukorrhea | 0.2% of women
Incidence <1% but >0.1% | Moniliasis | 0.2%
Incidence <1% but >0.1% | Pruritus | 0.2%
Incidence <1% but >0.1% | Somnolence | 0.2%
a1733 males, 2108 females

The following laboratory value changes of possible clinical significance, irrespective of relationship to therapy with cefdinir, were seen during clinical trials conducted in the U.S.:

LABORATORY VALUE CHANGES OBSERVED WITH CEFDINIR CAPSULESU.S. TRIALS IN ADULT AND ADOLESCENT PATIENTS (N = 3841)
Incidence ≥1% | ↑Urine leukocytes | 2%
Incidence ≥1% | ↑Urine protein | 2%
Incidence ≥1% | ↑Gamma-glutamyltransferasea | 1%
Incidence ≥1% | ↓Lymphocytes, ↑Lymphocytes | 1%, 0.2%
Incidence ≥1% | ↑Microhematuria | 1%
Incidence <1% but >0.1% | ↑Glucosea | 0.9%
Incidence <1% but >0.1% | ↑Urine glucose | 0.9%
Incidence <1% but >0.1% | ↑White blood cells, ↓White blood cells | 0.9%, 0.7%
Incidence <1% but >0.1% | ↑Alanine aminotransferase (ALT) | 0.7%
Incidence <1% but >0.1% | ↑Eosinophils | 0.7%
Incidence <1% but >0.1% | ↑Urine specific gravity, ↓Urine specific gravitya | 0.6%, 0.2%
Incidence <1% but >0.1% | ↓Bicarbonatea | 0.6%
Incidence <1% but >0.1% | ↑Phosphorus, ↓Phosphorusa | 0.6%, 0.3%
Incidence <1% but >0.1% | ↑Aspartate aminotransferase (AST) | 0.4%
Incidence <1% but >0.1% | ↑Alkaline phosphatase | 0.3%
Incidence <1% but >0.1% | ↑Blood urea nitrogen (BUN) | 0.3%
Incidence <1% but >0.1% | ↓Hemoglobin | 0.3%
Incidence <1% but >0.1% | ↑Polymorphonuclear neutrophils (PMNs), ↓PMNs | 0.3%, 0.2%
Incidence <1% but >0.1% | ↑Bilirubin | 0.2%
Incidence <1% but >0.1% | ↑Lactate dehydrogenasea | 0.2%
Incidence <1% but >0.1% | ↑Platelets | 0.2%
Incidence <1% but >0.1% | ↑Potassiuma | 0.2%
Incidence <1% but >0.1% | ↑Urine pHa | 0.2%
aN <3841 for these parameters

Clinical Trials - Cefdinir for Oral Suspension (Pediatric Patients)

In clinical trials, 2289 pediatric patients (1783 U.S. and 506 non-U.S.) were treated with the recommended dose of cefdinir suspension (14 mg/kg/day). Most adverse events were mild and self-limiting. No deaths or permanent disabilities were attributed to cefdinir. Forty of 2289 (2%) patients discontinued medication due to adverse events considered by the investigators to be possibly, probably, or definitely associated with cefdinir therapy. Discontinuations were primarily for gastrointestinal disturbances, usually diarrhea. Five of 2289 (0.2%) patients were discontinued due to rash thought related to cefdinir administration.

In the U.S., the following adverse events were thought by investigators to be possibly, probably, or definitely related to cefdinir suspension in multiple-dose clinical trials (N = 1783 cefdinir-treated patients):

ADVERSE EVENTS ASSOCIATED WITH CEFDINIR SUSPENSION U.S. TRIALS IN PEDIATRIC PATIENTS (N = 1783)a
Incidence ≥1% | Diarrhea | 8%
Incidence ≥1% | Rash | 3%
Incidence ≥1% | Vomiting | 1%
Incidence <1% but >0.1% | Cutaneous moniliasis | 0.9%
Incidence <1% but >0.1% | Abdominal pain | 0.8%
Incidence <1% but >0.1% | Leukopeniab | 0.3%
Incidence <1% but >0.1% | Vaginal moniliasis | 0.3% of girls
Incidence <1% but >0.1% | Vaginitis | 0.3% of girls
Incidence <1% but >0.1% | Abnormal stools | 0.2%
Incidence <1% but >0.1% | Dyspepsia | 0.2%
Incidence <1% but >0.1% | Hyperkinesia | 0.2%
Incidence <1% but >0.1% | Increased ASTb | 0.2%
Incidence <1% but >0.1% | Maculopapular rash | 0.2%
Incidence <1% but >0.1% | Nausea | 0.2%
a977 males, 806 females
bLaboratory changes were occasionally reported as adverse events.

NOTE: In both cefdinir- and control-treated patients, rates of diarrhea and rash were higher in the youngest pediatric patients. The incidence of diarrhea in cefdinir-treated patients ≤2 years of age was 17% (95/557) compared with 4% (51/1226) in those >2 years old. The incidence of rash (primarily diaper rash in the younger patients) was 8% (43/557) in patients ≤2 years of age compared with 1% (8/1226) in those >2 years old.

The following laboratory value changes of possible clinical significance, irrespective of relationship to therapy with cefdinir, were seen during clinical trials conducted in the U.S.:

LABORATORY VALUE CHANGES OF POSSIBLE CLINICAL SIGNIFICANCE OBSERVED WITH CEFDINIR SUSPENSION U.S. TRIALS IN PEDIATRIC PATIENTS (N = 1783)
Incidence ≥1% | ↑Lymphocytes, ↓Lymphocytes | 2%, 0.8%
Incidence ≥1% | ↑Alkaline phosphatase | 1%
Incidence ≥1% | ↓Bicarbonatea | 1%
Incidence ≥1% | ↑Eosinophils | 1%
Incidence ≥1% | ↑Lactate dehydrogenase | 1%
Incidence ≥1% | ↑Platelets | 1%
Incidence ≥1% | ↑PMNs, ↓PMNs | 1%, 1%
Incidence ≥1% | ↑Urine protein | 1%
Incidence <1% but >0.1% | ↑Phosphorus, ↓Phosphorus | 0.9%, 0.4%
Incidence <1% but >0.1% | ↑Urine pH | 0.8%
Incidence <1% but >0.1% | ↓White blood cells, ↑White blood cells | 0.7%, 0.3%
Incidence <1% but >0.1% | ↓Calciuma | 0.5%
Incidence <1% but >0.1% | ↓Hemoglobin | 0.5%
Incidence <1% but >0.1% | ↑Urine leukocytes | 0.5%
Incidence <1% but >0.1% | ↑Monocytes | 0.4%
Incidence <1% but >0.1% | ↑AST | 0.3%
Incidence <1% but >0.1% | ↑Potassiuma | 0.3%
Incidence <1% but >0.1% | ↑Urine specific gravity, ↓Urine specific gravity | 0.3%, 0.1%
Incidence <1% but >0.1% | ↓Hematocrita | 0.2%
aN = 1387 for these parameters

Postmarketing Experience

The following adverse experiences and altered laboratory tests, regardless of their relationship to cefdinir, have been reported during extensive postmarketing experience, beginning with approval in Japan in 1991: shock, anaphylaxis with rare cases of fatality, facial and laryngeal edema, feeling of suffocation, serum sickness-like reactions, conjunctivitis, stomatitis, Stevens-Johnson syndrome, toxic epidermal necrolysis, exfoliative dermatitis, erythema multiforme, erythema nodosum, acute hepatitis, cholestasis, fulminant hepatitis, hepatic failure, jaundice, increased amylase, acute enterocolitis, bloody diarrhea, hemorrhagic colitis, melena, pseudomembranous colitis, pancytopenia, granulocytopenia, leukopenia, thrombocytopenia, idiopathic thrombocytopenic purpura, hemolytic anemia, acute respiratory failure, asthmatic attack, drug-induced pneumonia, eosinophilic pneumonia, idiopathic interstitial pneumonia, fever, acute renal failure, nephropathy, bleeding tendency, coagulation disorder, disseminated intravascular coagulation, upper GI bleed, peptic ulcer, ileus, loss of consciousness, allergic vasculitis, possible cefdinir-diclofenac interaction, cardiac failure, chest pain, myocardial infarction, hypertension, involuntary movements, and rhabdomyolysis.

Cephalosporin Class Adverse Events

The following adverse events and altered laboratory tests have been reported for cephalosporin-class antibiotics in general:
Allergic reactions, anaphylaxis, Stevens-Johnson syndrome, erythema multiforme, toxic epidermal necrolysis, renal dysfunction, toxic nephropathy, hepatic dysfunction including cholestasis, aplastic anemia, hemolytic anemia, hemorrhage, false-positive test for urinary glucose, neutropenia, pancytopenia, and agranulocytosis. Pseudomembranous colitis symptoms may begin during or after antibiotic treatment (see WARNINGS).
Several cephalosporins have been implicated in triggering seizures, particularly in patients with renal impairment when the dosage was not reduced (see DOSAGE AND ADMINISTRATIONand OVERDOSAGE). If seizures associated with drug therapy occur, the drug should be discontinued. Anticonvulsant therapy can be given if clinically indicated.

OVERDOSAGE

Information on cefdinir overdosage in humans is not available. In acute rodent toxicity studies, a single oral 5600 mg/kg dose produced no adverse effects. Toxic signs and symptoms following overdosage with other β-lactam antibiotics have included nausea, vomiting, epigastric distress, diarrhea, and convulsions. Hemodialysis removes cefdinir from the body. This may be useful in the event of a serious toxic reaction from overdosage, particularly if renal function is compromised.

DOSAGE AND ADMINISTRATION

(see INDICATIONS AND USAGEfor Indicated Pathogens)
The recommended dosage and duration of treatment for infections in adults and adolescents are described in the following chart; the total daily dose for all infections is 600 mg. Once-daily dosing for 10 days is as effective as BID dosing. Once-daily dosing has not been studied in pneumonia or skin infections; therefore, cefdinir capsules should be administered twice daily in these infections. Cefdinir capsules may be taken without regard to meals.

Adults and Adolescents (Age 13 Years and Older)
Type of Infection | Dosage | Duration
Community-Acquired Pneumonia | 300 mg q12h | 10 days
Acute Exacerbations of Chronic Bronchitis | 300 mg q12h or 600 mg q24h | 5 to 10 days 10 days
Acute Maxillary Sinusitis | 300 mg q12h or 600 mg q24h | 10 days 10 days
Pharyngitis/Tonsillitis | 300 mg q12h or 600 mg q24h | 5 to 10 days 10 days
Uncomplicated Skin and Skin Structure Infections | 300 mg q12h | 10 days

Patients With Renal Insufficiency

For adult patients with creatinine clearance <30 mL/min, the dose of cefdinir should be 300 mg given once daily.
Creatinine clearance is difficult to measure in outpatients. However, the following formula may be used to estimate creatinine clearance (CLcr) in adult patients. For estimates to be valid, serum creatinine levels should reflect steady-state levels of renal function.
Males: CLcr= (weight) (140 – age)
(72) (serum creatinine)
Females: CLcr= 0.85 x above value
where creatinine clearance is in mL/min, age is in years, weight is in kilograms, and serum creatinine is in mg/dL.^1
The following formula may be used to estimate creatinine clearance in pediatric patients:
CLcr= K x body length or height
serum creatinine
where K=0.55 for pediatric patients older than 1 year^2and 0.45 for infants (up to 1 year)^3.
In the above equation, creatinine clearance is in mL/min/1.73 m^2, body length or height is in centimeters, and serum creatinine is in mg/dL.
For pediatric patients with a creatinine clearance of <30 mL/min/1.73 m^2, the dose of cefdinir should be 7 mg/kg (up to 300 mg) given once daily.

Patients on Hemodialysis

Hemodialysis removes cefdinir from the body. In patients maintained on chronic hemodialysis, the recommended initial dosage regimen is a 300 mg or 7 mg/kg dose every other day. At the conclusion of each hemodialysis session, 300 mg (or 7 mg/kg) should be given. Subsequent doses (300 mg or 7 mg/kg) are then administered every other day.

HOW SUPPLIED

Cefdinir Capsules USP, 300 mg are lavender opaque/turquoise opaque size ‘0’ hard gelatin capsule filled with off-white to yellow powder and imprinted with ‘E99’ on turquoise opaque body with black ink.
Bottles of 10 NDC 72789-550-10
Store at20° to 25°C (68° to 77°F); excursions permitted to 15° to 30°C (59° to 86°F) [See USP Controlled Room Temperature]. Preserve in tight, light-resistant containers.

CLINICAL STUDIES

Community-Acquired Bacterial Pneumonia

In a controlled, double-blind study in adults and adolescents conducted in the U.S., cefdinir BID was compared with cefaclor 500 mg TID. Using strict evaluability and microbiologic/clinical response criteria 6 to 14 days posttherapy, the following clinical cure rates, presumptive microbiologic eradication rates, and statistical outcomes were obtained:

U.S. Community-Acquired Pneumonia Study Cefdinir vs Cefaclor
 | Cefdinir BID | Cefaclor TID | Outcome
Clinical Cure Rates | 150/187 (80%) | 147/186 (79%) | Cefdinir equivalent to control
Eradication Rates
Overall | 177/195 (91%) | 184/200 (92%) | Cefdinir equivalent to control
S. pneumoniae | 31/31 (100%) | 35/35 (100%)
H. influenzae | 55/65 (85%) | 60/72 (83%)
M. catarrhalis | 10/10 (100%) | 11/11 (100%)
H. parainfluenzae | 81/89 (91%) | 78/82 (95%)

In a second controlled, investigator-blind study in adults and adolescents conducted primarily in Europe, cefdinir BID was compared with amoxicillin/clavulanate 500/125 mg TID. Using strict evaluability and clinical response criteria 6 to 14 days posttherapy, the following clinical cure rates, presumptive microbiologic eradication rates, and statistical outcomes were obtained:

European Community-Acquired Pneumonia Study Cefdinir vs Amoxicillin/Clavulanate
 | Cefdinir BID | Amoxicillin/ Clavulanate TID | Outcome
Clinical Cure Rates | 83/104 (80%) | 86/97(89%) | Cefdinir not equivalent to control
Eradication Rates Overall | 85/96 (89%) | 84/90 (93%) | Cefdinir equivalent to control
S. pneumoniae | 42/44 (95%) | 43/44 (98%)
H. influenzae | 26/35 (74%) | 21/26 (81%)
M. catarrhalis | 6/6 (100%) | 8/8 (100%)
H. parainfluenzae | 11/11 (100%) | 12/12 (100%)

Streptococcal Pharyngitis/Tonsillitis

In four controlled studies conducted in the United States, cefdinir was compared with 10 days of penicillin in adult, adolescent, and pediatric patients. Two studies (one in adults and adolescents, the other in pediatric patients) compared 10 days of cefdinir QD or BID to penicillin 250 mg or 10 mg/kg QID. Using strict evaluability and microbiologic/clinical response criteria 5 to 10 days posttherapy, the following clinical cure rates, microbiologic eradication rates, and statistical outcomes were obtained:

Pharyngitis/Tonsillitis Studies Cefdinir (10 days) vs Penicillin (10 days)
Study | Efficacy Parameter | Cefdinir QD | Cefdinir BID | Penicillin QID | Outcome
Adults/ Adolescents | Eradication of S. pyogenes | 192/210 (91%) | 199/217 (92%) | 181/217 (83%) | Cefdinir superior to control
Adults/ Adolescents | Clinical Cure Rates | 199/210 (95%) | 209/217 (96%) | 193/217 (89%) | Cefdinir superior to control
Pediatric Patients | Eradication of S. pyogenes | 215/228 (94%) | 214/227 (94%) | 159/227 (70%) | Cefdinir superior to control
Pediatric Patients | Clinical Cure Rates | 222/228 (97%) | 218/227 (96%) | 196/227 (86%) | Cefdinir superior to control

Two studies (one in adults and adolescents, the other in pediatric patients) compared 5 days of cefdinir BID to 10 days of penicillin 250 mg or 10 mg/kg QID. Using strict evaluability and microbiologic/clinical response criteria 4 to 10 days posttherapy, the following clinical cure rates, microbiologic eradication rates, and statistical outcomes were obtained:

Pharyngitis/Tonsillitis Studies Cefdinir (5 days) vs Penicillin (10 days)
Study | Efficacy Parameter | Cefdinir BID | Penicillin QID | Outcome
Adults/ Adolescents | Eradication of S. pyogenes | 193/218 (89%) | 176/214 (82%) | Cefdinir equivalent to control
Adults/ Adolescents | Clinical Cure Rates | 194/218 (89%) | 181/214 (85%) | Cefdinir equivalent to control
Pediatric Patients | Eradication of S. pyogenes | 176/196 (90%) | 135/193 (70%) | Cefdinir superior to control
Pediatric Patients | Clinical Cure Rates | 179/196 (91%) | 173/193 (90%) | Cefdinir equivalent to control

REFERENCES

1. Cockcroft DW, Gault MH. Prediction of creatinine clearance from serum creatinine. Nephron 1976;16:31-41.
2. Schwartz GJ, Haycock GB, Edelmann CM, Spitzer A. A simple estimate of glomerular filtration rate in children derived from body length and plasma creatinine. Pediatrics 1976;58:259-63.
3. Schwartz GJ, Feld LG, Langford DJ. A simple estimate of glomerular filtration rate in full-term infants during the first year of life. J Pediatrics 1984;104:849-54.

Maalox®TC is a registered trademark of Novartis Consumer Health, Inc.
Clinitest® is a registered trademark of Miles, Inc.
Clinistix® is a registered trademark of Bayer Corporation.
Tes-Tape® is a registered trademark of Lilly Inc.
Distributed by:
Aurobindo Pharma USA, Inc.
279 Princeton-Hightstown Road
East Windsor, NJ 08520
Manufactured by:
Aurobindo Pharma Limited
Hyderabad-500 032, India
Revised: 10/2021

PACKAGE LABEL-PRINCIPAL DISPLAY PANEL - 300 mg

Rx only
Cefdinir
Capsules, USP
300 mg